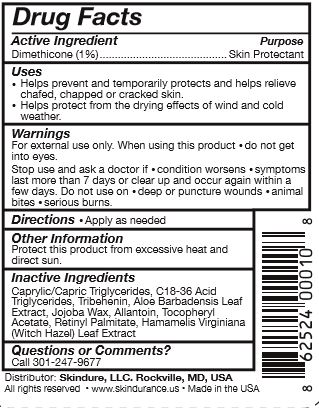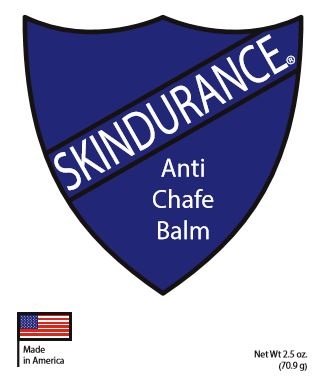 DRUG LABEL: Skindurance
NDC: 69802-025 | Form: STICK
Manufacturer: Skindure, LLC
Category: otc | Type: HUMAN OTC DRUG LABEL
Date: 20150430

ACTIVE INGREDIENTS: DIMETHICONE 1 mg/100 mg
INACTIVE INGREDIENTS: MEDIUM-CHAIN TRIGLYCERIDES; C18-36 ACID TRIGLYCERIDE; TRIBEHENIN; ALOE VERA LEAF; JOJOBA OIL; ALLANTOIN; .ALPHA.-TOCOPHEROL ACETATE; VITAMIN A PALMITATE; HAMAMELIS VIRGINIANA LEAF

Skindurance

Active Ingredient

Dimethicone (1%)

Purpose

Skin Protectant

Uses

• Helps prevent and temporarily protects and helps relieve chafed, chapped or cracked skin.

• Helps protect from the drying effects of wind and cold weather.

Warnings

For external use only. When using this product • do not get into eyes. Stop use and ask a doctor if • condition worsens • symptoms last more than 7 days or clear up and occur again within a few days. Do not use on • deep or puncture wounds • animal bites • serious burns.

Keep out of reach of children.

Directions

• Apply as needed

Inactive Ingredients

Caprylic/Capric Triglycerides, C18-36 Acid Triglycerides, Tribehenin, Aloe Barbadensis Leaf Extract, Jojoba Wax, Allantoin, Tocopheryl Acetate, Retinyl Palmitate, Hamamelis Virginiana (Witch Haxel) Leaf Extract

Other Information

Protect this product from excessive heat and direct sun.

Questions or Comments?

Call 301-247-9677